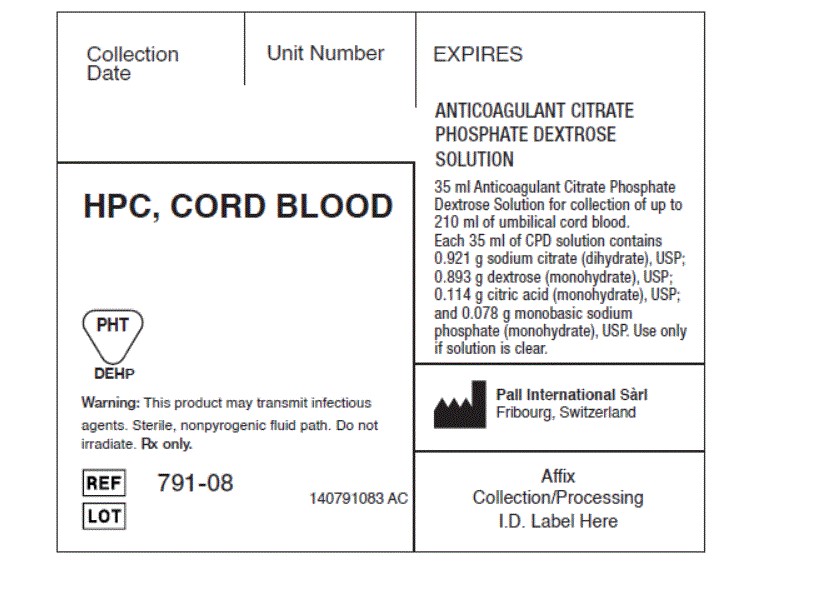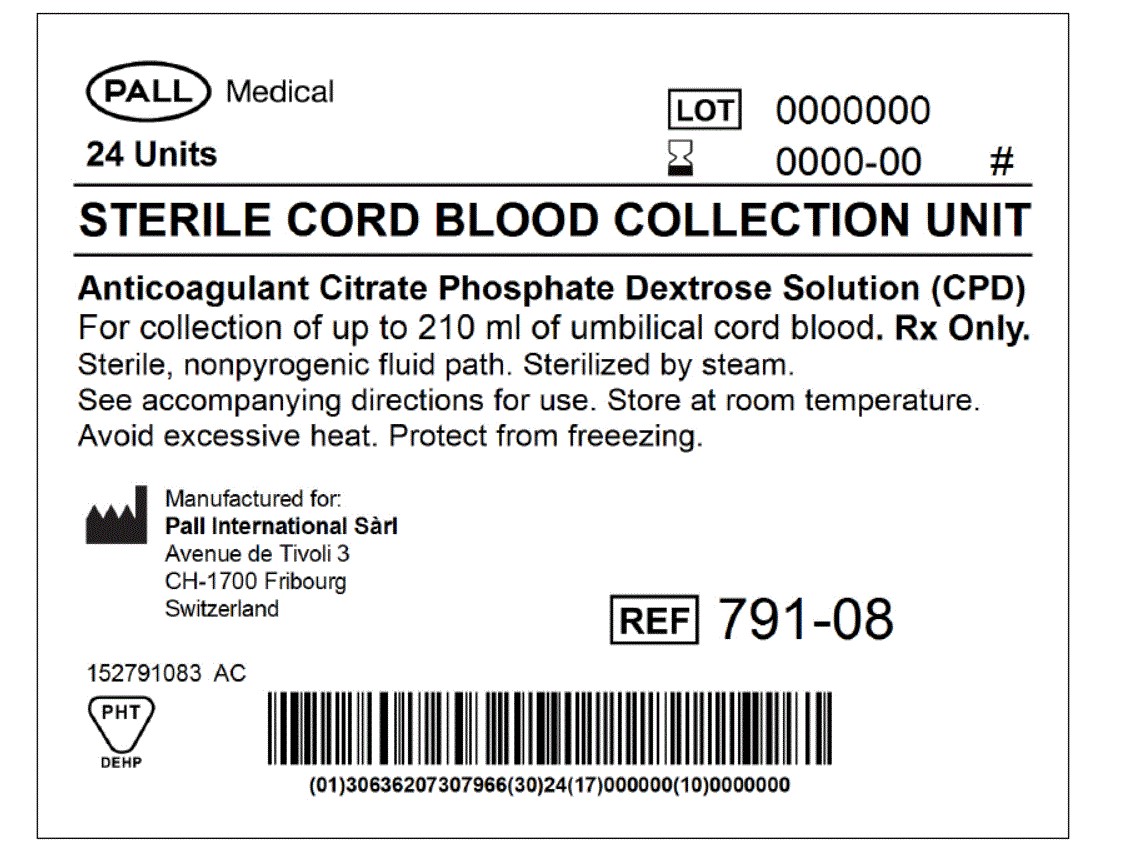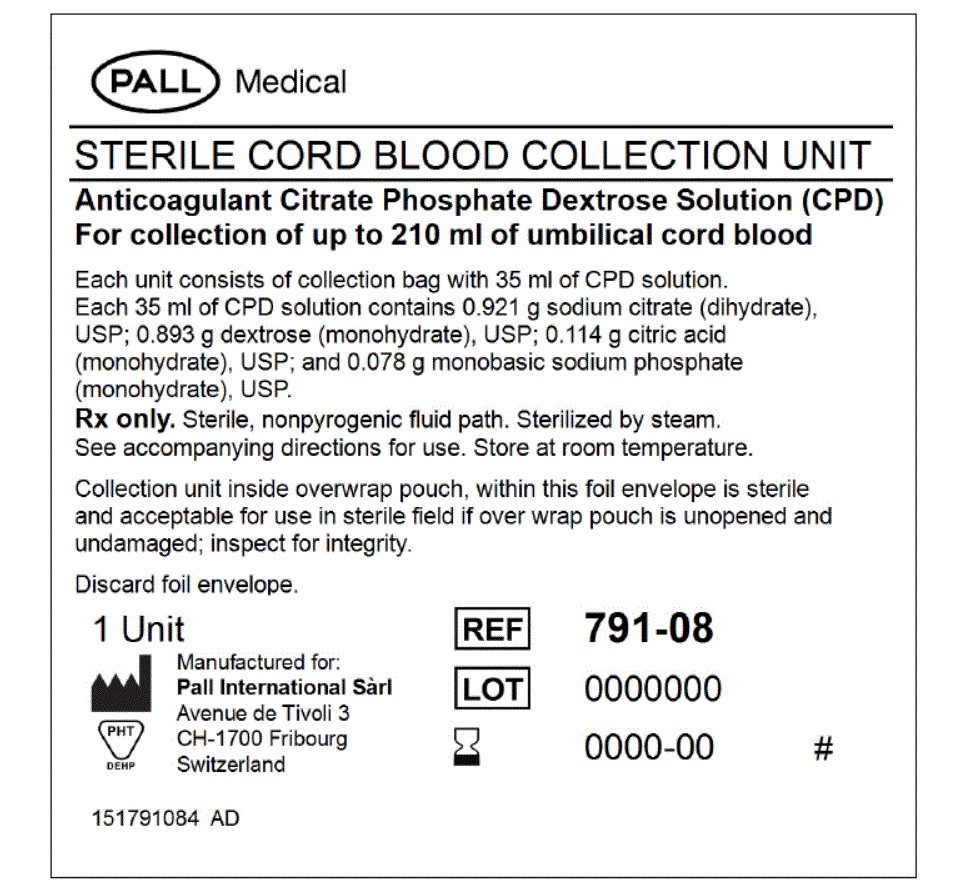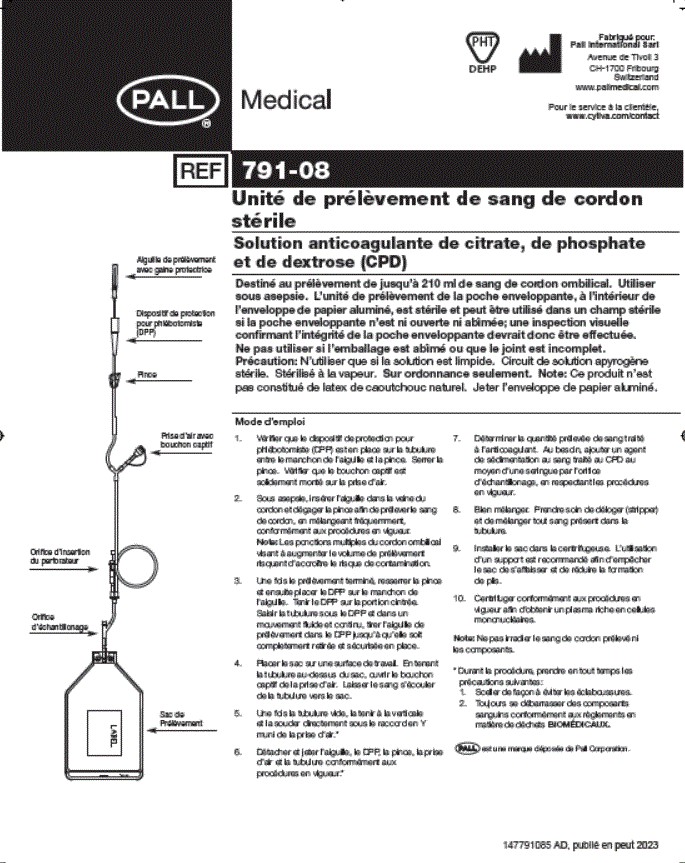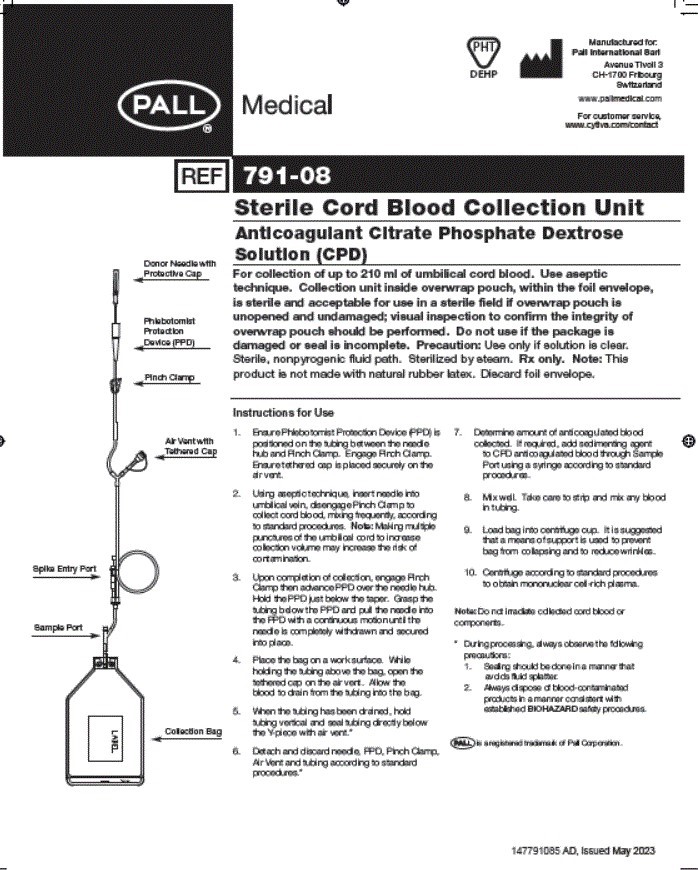 DRUG LABEL: Pall Sterile Cord Blood Collection Unit
NDC: 79403-791 | Form: SOLUTION
Manufacturer: Global Life Sciences Solutions USA LLC
Category: prescription | Type: HUMAN PRESCRIPTION DRUG LABEL
Date: 20251218

ACTIVE INGREDIENTS: SODIUM CITRATE 0.921 g/35 mL; CITRIC ACID MONOHYDRATE 0.114 g/35 mL; SODIUM PHOSPHATE, MONOBASIC, MONOHYDRATE 0.0078 g/35 mL; DEXTROSE MONOHYDRATE 0.893 g/35 mL
INACTIVE INGREDIENTS: WATER 35 g/35 mL; PHOSPHORIC ACID

CPD - 791-08

WARNINGS

Making multiple punctures of the umbilical cord to increase collection volume may increase the risk of contamination.

Do not irradiate collected cord blood or components.

HOW SUPPLIED

The Collection Unit inside the overwrap pouch, within the foil envelope, are sterile and acceptable for use in a sterile field if pouch is unopened and undamaged.

ANTICOAGULANT CITRATE PHOSPHATE DEXTROSE SOLUTION (CPD)

Sterile, non-pyrogenic fluid path. Sterilized by steam.

This product is free of natural rubber latex.

Indications and Usage Section

For collection of up to 210 ml of umbilical cord blood. Use aseptic technique.

Contents inside overwrap pouch, within the foil envelope, are sterile and acceptable for use in a sterile field if pouch is unopened and undamaged; visual inspection to confirm the integrity of overwrap pouch should be performed.

GENERAL PRECAUTIONS

Do not use if the package is damaged or seal is incomplete. Use only if solution is clear.
Sealing should be done in a manner that avoids fluid splatter.

Always dispose of blood-contaminated products in a manner consistent with established BIOHAZARD safety procedures.

INFORMATION FOR PATIENTS

For customer service, call: 1.800.645.6578

DonorCare is a registered trademark of ITL Corporation, Canberra, Australia. Produced under license from ThermoGenesis Corp

1. Ensure DonorCare® Needle Guard (DCNG) is positioned on the tubing between the needle hub and Pinch Clamp. Engage Pinch Clamp. Ensure tethered cap is placed securely on the air vent.
2. Using aseptic technique, insert needle into umbilical vein, disengage Pinch Clamp to collect cord blood, mixing frequently, according to standard procedures.
3. Upon completion of collection, engage Pinch Clamp then withdraw needle from umbilical vein. Slide the DCNG midway over the needle hub. While holding the sides of DCNG near front, grasp tubing and pull smoothly, pulling needle into the DCNG until it locks into place. Confirm that needle is locked by listening for the second click as the needle is drawn into the DCNG. Ensure that tubing cannot be pulled through DCNG.
4. Place the bag on a work surface. While holding the tubing above the bag, open the tethered cap on the air vent. Allow the blood to drain from the tubing into the bag.
5. When the tubing has been drained, hold tubing vertical and seal tubing directly below the Y-piece with air vent.
6. Detach and discard needle, DCNG, Pinch Clamp, Air Vent and tubing according to standard procedures.
7. Determine amount of anticoagulated blood collected. If required, add sedimenting agent to CPD anticoagulated blood through Sample Port using a syringe according to standard procedures.
8. Mix well. Take care to strip and mix any blood in tubing.
9. Load bag into centrifuge cup. It is suggested that a means of support is used to prevent bag from collapsing and to reduce wrinkles.
10. Centrifuge according to standard procedures to obtain mononuclear cell-rich plasma.